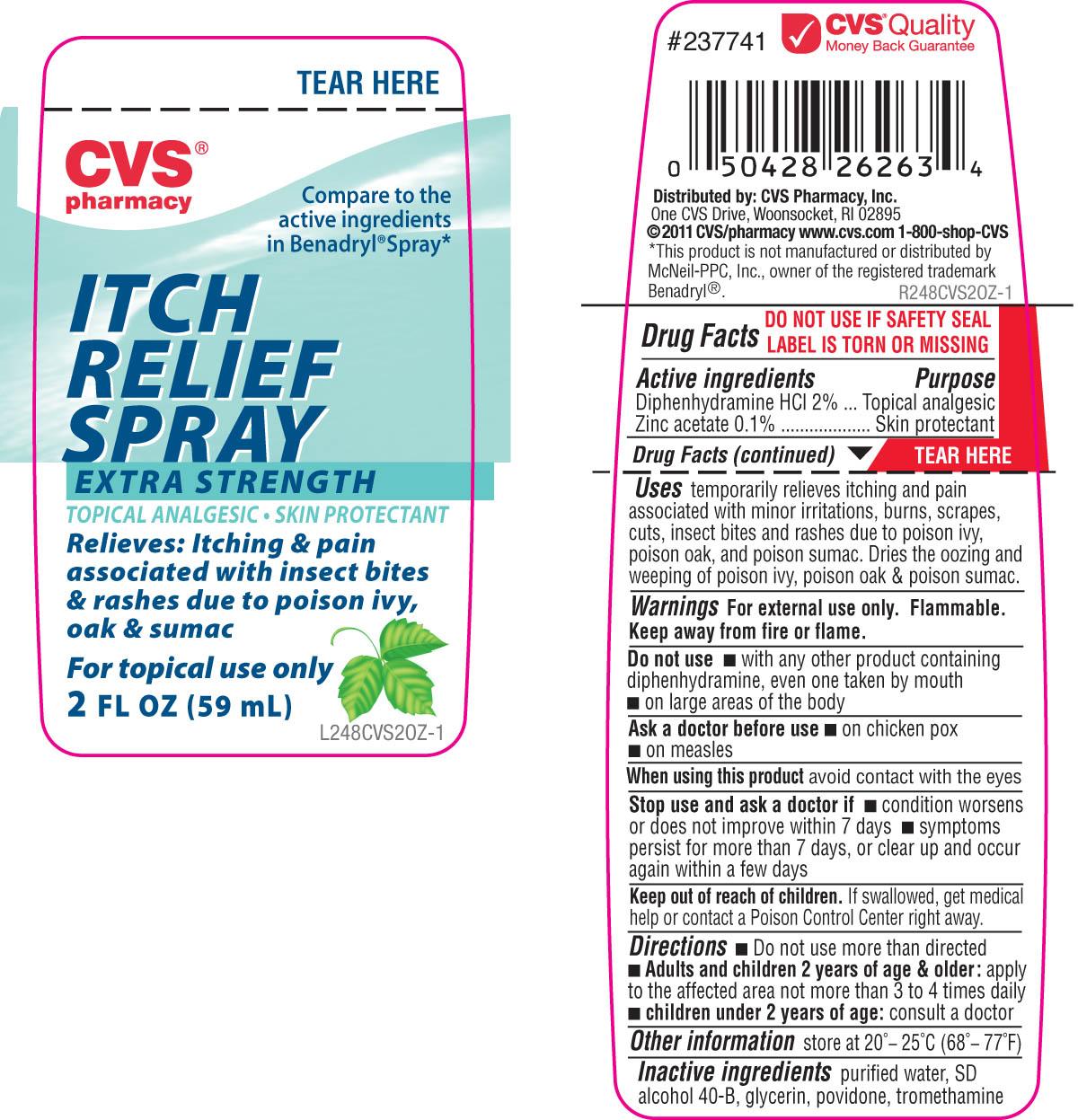 DRUG LABEL: CVS
NDC: 59779-248 | Form: SPRAY
Manufacturer: CVS Pharmacy
Category: otc | Type: HUMAN OTC DRUG LABEL
Date: 20120427

ACTIVE INGREDIENTS: DIPHENHYDRAMINE HYDROCHLORIDE 20 mg/1 mL; ZINC ACETATE 1 mg/1 mL
INACTIVE INGREDIENTS: WATER; ALCOHOL; GLYCERIN; POVIDONE; TROMETHAMINE

DRUG FACTS

Active ingredient Purpose
Diphenhydramine HCL 2% ...................................................................Topical analgesic
Zinc Acetate 0.1%...............................................................................Skin Protectant

Uses
Temporarily relieves itching and pain associated with minor irritations, burns,
scrapes, cuts, insect bites and rashes due to poison ivy, poison oak and poison
sumac. Dries the oozing and weeping of poison ivy, poison oak and poison sumac.

Keep out of reach of children. If swallowed, get medical help or contact a
Poison Control Center right away.

Uses
Temporarily relieves itching and pain associated with minor irritations, burns,
scrapes, cuts, insect bites and rashes due to poison ivy, poison oak and poison
sumac. Dries the oozing and weeping of poison ivy, poison oak and poison sumac.

Warnings
For external use only. Flammable. keep away from fire or flame.
Do not use - with any other product containing diphenhydramine,
even one taken by mouth. - On large areas of the body
Ask a doctor before use - on chicken pox - on measles
When using this product avoid contact with the eyes
Stop use and ask a doctor if condition worsens or does not improve within 7 days.
- symptoms persist for more than 7 days or clear up and occur again within a few days.
Keep out of reach of children. If swallowed, get medical help or contact a Poison Control Center right away.

Directions
- do not use more than directed
- Adults and children 2 years and older: apply to affected area not more than 3 to 4 times daily
- Children under 2 years of age: consult a doctor
Other information
Store at 20 degrees to 25 degrees C (68 degrees to 77 degrees F)

Inactive Ingredients
purified water, SD alcohol 40-B, glycerin, povidone, tromethamine